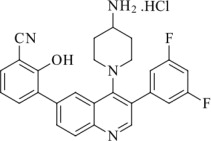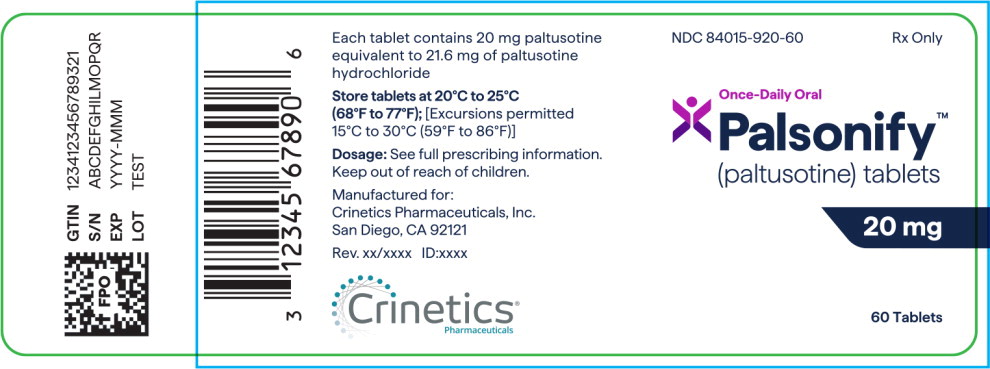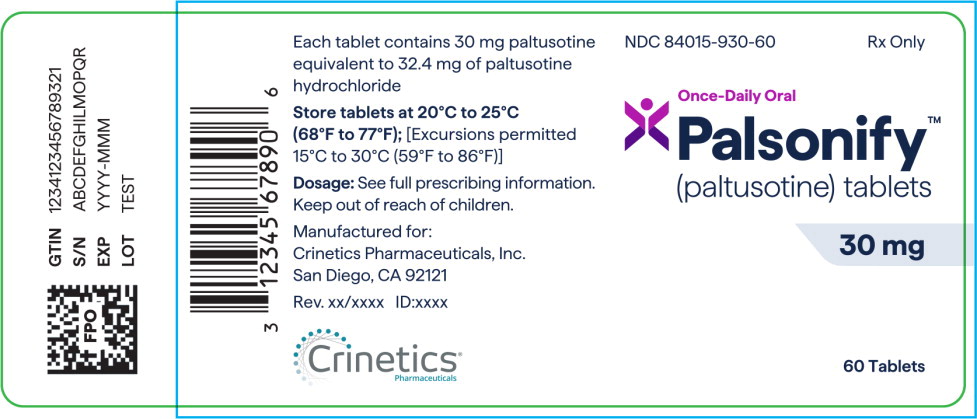 DRUG LABEL: PALSONIFY
NDC: 84015-920 | Form: TABLET, FILM COATED
Manufacturer: Crinetics Pharmaceuticals, Inc.
Category: prescription | Type: HUMAN PRESCRIPTION DRUG LABEL
Date: 20250916

ACTIVE INGREDIENTS: PALTUSOTINE HYDROCHLORIDE 20 mg/1 1
INACTIVE INGREDIENTS: COPOVIDONE K25-31; MANNITOL; MICROCRYSTALLINE CELLULOSE; CROSPOVIDONE, UNSPECIFIED; SILICON DIOXIDE; MAGNESIUM STEARATE; HYPROMELLOSE, UNSPECIFIED; TITANIUM DIOXIDE; TRIACETIN; FERRIC OXIDE YELLOW; FERRIC OXIDE RED

HIGHLIGHTS OF PRESCRIBING INFORMATION

These highlights do not include all the information needed to use PALSONIFY™ safely and effectively. See full prescribing information for PALSONIFY.
PALSONIFY (paltusotine) tablets, for oral use
Initial U.S. Approval: 2025

1 INDICATIONS AND USAGE

PALSONIFY is a somatostatin receptor agonist indicated for the treatment of adults with acromegaly who had an inadequate response to surgery and/or for whom surgery is not an option (1).

2 DOSAGE AND ADMINISTRATION

- Take orally once daily with water on an empty stomach (at least 6 hours after a meal) and at least 1 hour before the next meal (2.1).
- Recommended initial dosage is 40 mg once daily. During initiation, PALSONIFY may be temporarily reduced to 20 mg once daily if needed, based on tolerability. Once adverse reactions have resolved, resume PALSONIFY 40 mg once daily (2.2).
- After 2 to 4 weeks, based on IGF-1 levels, titrate to 60 mg once daily (2.2).

3 DOSAGE FORMS AND STRENGTHS

Tablets: 20 mg, 30 mg (3)

4 CONTRAINDICATIONS

- None (4)

5 WARNINGS AND PRECAUTIONS

- Cholelithiasis and its Complications: Monitor periodically. If complications of cholelithiasis occur, discontinue PALSONIFY and treat appropriately (5.1).
- Hyperglycemia and Hypoglycemia: Monitor glucose and adjust antidiabetic treatment as needed (5.2).
- Cardiovascular Abnormalities: Bradycardia or conduction abnormalities may occur. Dosage adjustments of concomitantly used drugs with bradycardia effects may be necessary (5.3).
- Thyroid Function Abnormalities: Hypothyroidism may occur. Assess thyroid function periodically (5.4).
- Steatorrhea and Malabsorption of Dietary Fats: New onset steatorrhea, stool discoloration, loose stools, abdominal bloating, and weight loss may occur. If new occurrence or worsening of these symptoms are reported, evaluate for potential pancreatic exocrine insufficiency (5.5).
- Vitamin B 12 Deficiency: Monitor vitamin B12 levels during treatment if indicated (5.6).

6 ADVERSE REACTIONS

Most common adverse reactions (≥5%) are diarrhea, abdominal pain, nausea, decreased appetite, sinus bradycardia, hyperglycemia, palpitations, and gastroenteritis (6.1).

To report SUSPECTED ADVERSE REACTIONS, contact Crinetics Pharmaceuticals, Inc. at toll-free phone 1-833-CRN-INFO or FDA at 1-800-FDA-1088 or www.fda.gov/medwatch.

7 DRUG INTERACTIONS

- Strong CYP3A4 Inducers: may decrease paltusotine exposure. May require PALSONIFY dosage increase (2.3, 7.1).
- Moderate CYP3A4 Inducers: may decrease paltusotine exposure. May require PALSONIFY dosage increase (2.3, 7.1).
- Proton Pump Inhibitors: may decrease paltusotine exposure. May require PALSONIFY dosage increase (2.3, 7.1)
- Cyclosporine: may decrease cyclosporine exposure. May require cyclosporine dosage adjustment (7.2).

FULL PRESCRIBING INFORMATION

1 INDICATIONS AND USAGE

PALSONIFY is indicated for the treatment of adults with acromegaly who had an inadequate response to surgery and/or for whom surgery is not an option.

2 DOSAGE AND ADMINISTRATION

2.1 Important Administration Instructions

- Take PALSONIFY orally once daily with water on an empty stomach, at least 6 hours after a meal (e.g., after overnight fasting) and at least 1 hour before the next meal [see Clinical Pharmacology (12.3)].

2.2 Recommended Dosage, Titration, and Monitoring

- The recommended initial dosage of PALSONIFY is 40 mg once daily.
- During initiation period, PALSONIFY may be temporarily reduced to 20 mg once daily if needed, based on tolerability [see Adverse Reactions (6.1)]. Once adverse reactions have resolved, resume PALSONIFY 40 mg once daily.
- After 2 to 4 weeks on PALSONIFY 40 mg once daily, based on IGF-1 levels, titrate to a PALSONIFY dosage of 60 mg once daily.

2.3 Dosage Modifications for Drug Interactions

Concomitant Use with Strong CYP3A4 Inducers

- Patients taking strong CYP3A4 inducers may require an increased dosage of PALSONIFY. Do not exceed three-fold the PALSONIFY dosage prior to concomitant use or 120 mg daily, whichever is less [see Drug Interactions (7.1)].

Concomitant Use with Moderate CYP3A4 Inducers

- Patients taking moderate CYP3A4 inducers may require an increased dosage of PALSONIFY. Do not exceed two-fold the PALSONIFY dosage prior to concomitant use or 120 mg daily, whichever is less [see Drug Interactions (7.1)].

Concomitant Use with Proton Pump Inhibitors

- Patients taking proton pump inhibitors may require an increased dosage of PALSONIFY. Avoid concomitant use of proton pump inhibitors in patients who are already on PALSONIFY 60 mg [see Drug Interactions (7.1)].

3 DOSAGE FORMS AND STRENGTHS

PALSONIFY Tablets:

- 20 mg: pink, biconvex oval tablets, debossed with “PAL” on one side and “20” on the other side; contains 20 mg paltusotine free base.
- 30 mg: yellow, biconvex oval tablets, debossed with “PAL” on one side and “30” on the other side; contains 30 mg paltusotine free base.

4 CONTRAINDICATIONS

None.

5 WARNINGS AND PRECAUTIONS

5.1 Cholelithiasis and its Complications

PALSONIFY may inhibit gallbladder contractility and decrease bile secretion, which may lead to gallbladder stones or sludge. Cholelithiasis was reported in participants treated with PALSONIFY in clinical trials. Complications of cholelithiasis, such as acute cholecystitis and pancreatitis, have also been reported with the use of PALSONIFY [see Adverse Reactions (6.1)]. Monitor patients periodically. If complications of cholelithiasis occur, discontinue PALSONIFY and treat appropriately.

5.2 Hyperglycemia and Hypoglycemia

PALSONIFY may alter the balance between the counter-regulatory hormones, insulin, glucagon, and growth hormone, which may result in hypoglycemia, hyperglycemia, or diabetes mellitus. Hyperglycemia was reported in participants treated with PALSONIFY in clinical trials [see Adverse Reactions (6.1)]. Monitor blood glucose levels when PALSONIFY treatment is initiated or when the dose is altered. Adjust antidiabetic treatment accordingly.

5.3 Cardiovascular Abnormalities

Cardiac conduction abnormalities and other ECG changes such as PR interval prolongation have occurred during treatment with PALSONIFY. Bradycardia, sinus arrest, and atrioventricular block were reported in participants treated with PALSONIFY in clinical trials [see Adverse Reactions (6.1)]. These ECG changes may occur in patients with acromegaly. Dosage adjustments of concomitantly used drugs that have bradycardia effects (e.g., beta-blockers) may be necessary.

5.4 Thyroid Function Abnormalities

Somatostatin analogs may suppress the secretion of thyroid-stimulating hormone, which may result in hypothyroidism. Periodic assessment of thyroid function (TSH, total, and/or free T4) is recommended during treatment with PALSONIFY.

5.5 Steatorrhea and Malabsorption of Dietary Fats

New onset steatorrhea, stool discoloration and loose stools have been reported in patients receiving somatostatin analogs. Somatostatin analogs reversibly inhibit secretion of pancreatic enzymes and bile acids, which may result in malabsorption of dietary fats and subsequent symptoms of steatorrhea, loose stools, abdominal bloating, and weight loss. If new occurrence or worsening of these symptoms are reported in patients receiving PALSONIFY, evaluate patients for potential pancreatic exocrine insufficiency and manage accordingly.

5.6 Vitamin B12 Deficiency

Decreased vitamin B12 levels have been observed in patients treated with somatostatin analogs, including PALSONIFY. Monitor vitamin B12 levels during treatment with PALSONIFY if clinically indicated.

6 ADVERSE REACTIONS

The following clinically significant adverse reactions are described elsewhere in the labeling:

- Cholelithiasis and Complications of Cholelithiasis [see Warnings and Precautions (5.1)]
- Hyperglycemia and Hypoglycemia [see Warnings and Precautions (5.2)]
- Cardiovascular Abnormalities [see Warnings and Precautions (5.3)]
- Thyroid Function Abnormalities [see Warnings and Precautions (5.4)]
- Steatorrhea and Malabsorption of Dietary Fats [see Warnings and Precautions (5.5)]
- Changes in Vitamin B12 Levels [see Warnings and Precautions (5.6)]

6.1 Clinical Trials Experience

Because clinical trials are conducted under widely varying conditions, adverse reaction rates observed in the clinical trials of a drug cannot be directly compared to rates in the clinical trials of another drug and may not reflect the rates observed in practice.

The safety of PALSONIFY was evaluated in adults with acromegaly in two randomized, double-blind, placebo-controlled Phase 3 studies. Study 1 was a 24-week, randomized, placebo-controlled study in 111 adults who were naive or previously treated on a somatostatin analog and biochemically uncontrolled at randomization. Participants in Study 1 had a mean age of 47 years (range: 18 to 80 years) and were randomized to PALSONIFY (n=54) or placebo (n=57) [see Clinical Studies (14.1)]. Study 2 was a 36-week, randomized, placebo-controlled study in 58 adults who were biochemically controlled on injectable depot formulations of octreotide or lanreotide. Participants in Study 2 had a mean age of 55 years (range: 29 to 84 years) and were randomized to PALSONIFY (n=30) or placebo (n=28) [see Clinical Studies (14.2)].

Adverse Reactions

Adverse reactions that occurred in ≥5% of PALSONIFY-treated participants and 5% greater incidence than placebo in the randomized-controlled phase of Study 1 and Study 2 are presented in Table 1 and Table 2, respectively. Adverse reactions presented in Table 1 and Table 2 exclude events which occurred after a participant received rescue therapy (Study 1 PALSONIFY n=1, placebo n=13; Study 2 PALSONIFY n=1, placebo n=17).

Table 1. Adverse Reactions Occurring in ≥5% of PALSONIFY-Treated Participants and 5% Greater Incidence than Placebo-Treated Participants During the Randomized Controlled Period of Study 1
Adverse Reaction | PALSONIFY N=54 n (%) | Placebo N=57 n (%)
Diarrhea | 18 (33) | 8 (14)
Abdominal paina | 10 (19) | 3 (5)
Nausea | 5 (9) | 1 (2)
Sinus bradycardia | 4 (7) | 0
Hyperglycemiab | 4 (7) | 1 (2)
a Abdominal pain also includes abdominal discomfort.
b Hyperglycemia also includes impaired fasting glucose and diabetes mellitus.

Table 2. Adverse Reactions Occurring in ≥5% of PALSONIFY-Treated Participants and 5% Greater Incidence than Placebo-Treated Participants During the Randomized Controlled Period of Study 2
Adverse Reaction | PALSONIFY N=30 n (%) | Placebo N=28 n (%)
Diarrhea | 7 (23) | 3 (11)
Nausea | 4 (13) | 1 (4)
Decreased appetitea | 3 (10) | 0
Palpitations | 2 (7) | 0
Gastroenteritis | 2 (7) | 0
a Decreased appetite also includes early satiety.

Gastrointestinal

Gastrointestinal adverse reactions, including diarrhea, nausea, and abdominal pain were reported in participants from Studies 1 and 2 (see Table 1 and Table 2). Most gastrointestinal adverse reactions occurred within the first two months of PALSONIFY treatment initiation and had a median duration ranging between 6 to 18 days.

Other Adverse Reactions from Studies 1 and 2

Cholelithiasis and its Complications

Cholelithiasis and its complications were reported in 10/173 (6%) participants during Studies 1 and 2 as follows: cholelithiasis (n=8), acute cholecystitis, biliary colic, and bile duct stone (one participant each). The majority of the events occurred within the first nine months of treatment. One PALSONIFY-treated participant who experienced obstructive pancreatitis required cholecystectomy [see Warnings and Precautions (5.1)].

Glucose Metabolism

Hyperglycemia

During Study 1, an increase from baseline to Week 24 in mean fasting plasma glucose (FPG) of 6.9 mg/dL and hemoglobin A1c (HbA1c) of 0.26% was observed in the PALSONIFY arm, and an increase in mean FPG of 1.5 mg/dL and HbA1c of 0.04% was observed in the placebo arm. Of the 34 PALSONIFY-treated participants who had normal baseline FPG, 25 (74%) developed at least one glucose value ≥100 mg/dL. Of the 31 placebo-treated participants who had a normal baseline FPG, 9 (29%) developed at least one elevated glucose value.

All participants in Study 2 were previously treated with other somatostatin analog products known to increase glucose levels. During Study 2, a decrease from baseline to Week 36 in mean FPG of 1.8 mg/dL and HbA1c of 0.05% was observed in the PALSONIFY arm, and a decrease in mean FPG of 11.7 mg/dL and HbA1c of 0.25% was observed in the placebo arm. Of the 5 PALSONIFY-treated participants who had normal baseline FPG, 4 (80%) developed at least one glucose value ≥100 mg/dL. Of the 11 placebo-treated participants who had a normal baseline FPG, 2 (18%) developed at least one elevated glucose value.

Hypoglycemia

During PALSONIFY clinical development program, 5 participants in the open-label extension phase reported hypoglycemia. Most participants had a history of diabetes at baseline and were treated with antidiabetic medications, such as insulin and sulfonylureas.

Cardiac

Bradycardia was reported in 4 (7%) participants in the paltusotine arm versus none in placebo in Study 1, and in 1 (3%) participant in the paltusotine arm versus none in placebo in Study 2. Bradycardia was asymptomatic and occurred within the first three months of treatment.

During the PALSONIFY clinical development program, 3 PALSONIFY-treated participants with preexisting cardiovascular comorbidities experienced serious cardiac adverse events during the open-label extension phase: sinus arrest (2 participants) and complete atrioventricular block (one participant).

Ocular

Findings of ocular phototoxicity were observed in a nonclinical study [see Nonclinical Toxicology (13.2)]. Due to these findings, ocular assessments were conducted during the open-label period of Studies 1 and 2. The following retinal observations were noted: drusen; dry age-related macular degeneration, early stage; retinal pigment epithelium changes; epiretinal membrane; diabetic retinopathy; retinoschisis; and hypertensive retinopathy. Baseline assessments were not available for comparison.

7 DRUG INTERACTIONS

7.1 Effect of Other Drugs on PALSONIFY

Table 3. Clinically Significant Interactions Affecting PALSONIFY
Strong CYP3A4 Inducers
Intervention | Concomitant use of PALSONIFY with strong CYP3A4 inducers may require an increased dosage of PALSONIFY, not to exceed three-fold the dose prior to concomitant use or 120 mg daily, whichever is less.
Clinical Impact | Concomitant use of PALSONIFY with strong CYP3A4 inducers reduced paltusotine exposure and may affect therapeutic response [see Clinical Pharmacology (12.3)].
Moderate CYP3A4 Inducers
Intervention | Concomitant use of PALSONIFY with moderate CYP3A4 inducers may require an increased dosage of PALSONIFY, not to exceed two-fold the dose prior to concomitant use or 120 mg daily, whichever is less.
Clinical Impact | Concomitant use of PALSONIFY with moderate CYP3A4 inducers resulted in a decrease in paltusotine exposure [see Clinical Pharmacology (12.3)].
Proton Pump Inhibitors
Intervention | Concomitant use of PALSONIFY with PPIs may require an increased dosage of PALSONIFY. Patients who are already on PALSONIFY 60 mg should avoid concomitant use with proton pump inhibitors.
Clinical Impact | Concomitant use of PALSONIFY with proton pump inhibitors demonstrated a dose-dependent decrease in paltusotine exposure [see Clinical Pharmacology (12.3)].

7.2 Effect of PALSONIFY on Other Drugs

Table 4. Clinically Significant Interactions Affecting Other Drugs
Cyclosporine
Intervention | Adjustment of cyclosporine dose to maintain therapeutic levels may be necessary. Follow recommended therapeutic drug monitoring for cyclosporine.
Clinical Impact | Concomitant use of PALSONIFY with cyclosporine resulted in a decrease in cyclosporine bioavailability [see Clinical Pharmacology (12.3)].

8 USE IN SPECIFIC POPULATIONS

8.1 Pregnancy

Risk Summary

The available data with PALSONIFY use in pregnant women are insufficient to identify a drug-associated risk of major birth defects, miscarriage, or other adverse maternal or fetal outcomes. In animal reproduction studies, no malformations were observed with oral administration of paltusotine to pregnant rats and rabbits during organogenesis at exposures 11 and 3 times the human exposure at the maximum recommended human dose (MRHD) of 60 mg once daily, respectively (see Data).

The background risk of major birth defects and miscarriage for the indicated population is unknown. All pregnancies have a background risk of birth defect, loss, or other adverse outcomes. In the U.S. general population, the background risk of major birth defects and miscarriage in clinically recognized pregnancies is 2% to 4% and 15% to 20%, respectively.

Data

Animal Data

In an embryo-fetal development study in pregnant rats, paltusotine was administered orally at 25, 75, and 500 mg/kg/day during the period of organogenesis from gestation Day 7 to 17. The NOAEL for maternal and embryo-fetal developmental toxicity was 500 mg/kg/day, as no paltusotine-related effects were observed on any ovarian, uterine or litter parameters (approximately 11 times the MRHD based on AUC).

In an embryo-fetal development study in pregnant rabbits, paltusotine was administered orally at 10, 25, and 75 mg/kg/day during the period of organogenesis from gestation Day 7 to 19. Maternal findings included an increased incidence of spontaneous abortions at 75 mg/kg/day, with decreased body weight gain, body weights, and food consumption. No fetal abnormalities were observed at any dose. Lower fetal body weight was noted at 75 mg/kg/day. The NOAEL for maternal and embryo-fetal developmental toxicity was 25 mg/kg/day (approximately 3 times the MRHD based on AUC).

In a pre- and postnatal development study, pregnant rats were given paltusotine orally at the doses of 25, 75, and 500 mg/kg/day from gestation Day 6 to lactation Day 20. Paltusotine had no effect on the growth and development of offspring up to the highest tested dose of 500 mg/kg (5 times MRHD based on AUC). In a single dose pharmacokinetic study, oral administration of paltusotine at 25 mg/kg or 500 mg/kg paltusotine to pregnant rats showed measurable paltusotine concentrations in embryos and fetuses, demonstrating placental transfer. Overall, the embryo and fetal concentrations were generally low when compared to maternal concentrations.

8.2 Lactation

Risk Summary

There is no information available on the presence of paltusotine in human milk, the effects of the drug on the breastfed infant, or the effects of the drug on milk production. Paltusotine is present in animal milk (see Data). When a drug is present in animal milk, it is likely that the drug will be present in human milk. The developmental and health benefits of breastfeeding should be considered along with the mother's clinical need for PALSONIFY and any potential adverse effects on the breastfed infant from PALSONIFY or from the underlying maternal condition.

Data

Paltusotine concentrations were elevated 2.4- to 3.8-fold in rat milk compared to plasma during animal studies. Paltusotine concentrations in plasma and maternal milk suggest that rat pups were likely exposed in utero and/or via lactational transfer. The concentration of paltusotine in animal milk does not necessarily predict the concentration of paltusotine in human milk.

8.4 Pediatric Use

The safety and efficacy of PALSONIFY have not been established in pediatric patients.

8.5 Geriatric Use

In the Phase 3 studies 17/84 (20.2%) PALSONIFY-treated participants were ≥65 years of age. No overall differences in safety or effectiveness of PALSONIFY have been observed between participants 65 years of age and older and younger adult participants. No dose adjustments are required based on age [see Clinical Pharmacology (12.3)].

8.6 Hepatic Impairment

No dosage adjustment of PALSONIFY is recommended for patients with hepatic impairment. In a clinical pharmacology study in participants with varying degrees of hepatic impairment, exposures of paltusotine were similar across all hepatic impairment groups when compared with participants with normal hepatic function [see Clinical Pharmacology (12.3)].

10 OVERDOSAGE

Overdose with somatostatin analogs may result in hyperglycemia or hypoglycemia, bradycardia, arrhythmia, diarrhea, vomiting, and other gastrointestinal symptoms. If overdose is suspected, initiate supportive treatment as dictated by patient's clinical status.

11 DESCRIPTION

PALSONIFY tablets contain paltusotine hydrochloride, a somatostatin receptor agonist. Paltusotine is known chemically as 3-[4-(4-Amino-1-piperidinyl)-3-(3,5-difluorophenyl)-6-quinolinyl]-2-hydroxybenzonitrile hydrochloride. The molecular weight of paltusotine hydrochloride is 492.95 g/mol (C27H22F2N4O·HCl).

PALSONIFY tablets for oral administration contain 20 mg of paltusotine (equivalent to 21.6 mg of paltusotine hydrochloride) or 30 mg of paltusotine (equivalent to 32.4 mg of paltusotine hydrochloride). Each tablet contains the following inactive ingredients: colloidal silicon dioxide, copovidone, crospovidone, magnesium stearate, mannitol, and microcrystalline cellulose. Additionally, the 20 mg tablets contain Opadry pink coating (hypromellose, iron oxide red, iron oxide yellow, titanium dioxide, and triacetin) and the 30 mg tablets contain Opadry yellow coating (hypromellose, iron oxide yellow, titanium dioxide, and triacetin).

12 CLINICAL PHARMACOLOGY

12.1 Mechanism of Action

Similar to the natural hormone somatostatin, paltusotine suppresses growth hormone (GH) and insulin-like growth factor-1 (IGF-1) secretion. Paltusotine exerts its pharmacological activity via selective agonism (>4000-fold) at somatostatin receptor 2 (SSTR2) and exhibits little or no affinity for other SST receptor subtypes. Paltusotine inhibited cyclic adenosine monophosphate accumulation via human SSTR2 activation with an average drug (agonist) concentration that results in half-maximal response (EC50) of 0.25 nM.

12.2 Pharmacodynamics

In patients with acromegaly, there was a dose-dependent reduction in IGF-1 levels over the therapeutic dose range of 20 to 60 mg.

Paltusotine may inhibit gallbladder contractility and decrease bile secretion, which may lead to gallbladder stones or sludge [see Warnings and Precautions (5.1)].

Cardiac Electrophysiology

At 4.6 times the maximum recommended dose of PALSONIFY, clinically significant QTc interval prolongation was not observed.

12.3 Pharmacokinetics

Paltusotine exhibited dose-proportional increases in exposures for doses ranging from 20 mg (lowest approved recommended dosage) to 120 mg (2 times the highest approved recommended dosage) in healthy participants. Apparent dose proportional increase was observed for mean steady-state trough concentrations up to 60 mg once daily in participants with acromegaly. Following once daily administration, paltusotine reaches steady-state exposure within one week.

Absorption

Following oral administration of paltusotine, the median time to maximum plasma concentration (tmax) is 1 to 4 hours regardless of post dose fasting duration.

Effect of Food

Relative to administration in the fasted state, administration of paltusotine with a high-fat meal (800 to 1000 calories, 50% to 60% fat) reduced the AUC by 85% and the Cmax by 81%. Administration of paltusotine with a low-fat meal (400 to 500 calories, 25% fat) reduced AUC by 72% and the Cmax by 68%.

Distribution

The volume of distribution (Vz) of paltusotine is 220 L. Paltusotine is highly plasma protein bound (99%).

Elimination

After maximal concentrations were attained, paltusotine concentration declined with apparent terminal half-life (t½) of 28 hours.

Metabolism

Paltusotine is metabolized primarily in the liver via glucuronidation and oxidation. In vitro, glucuronidation was the major metabolic pathway and is primarily mediated by UGT1A1 and UGT1A9. Oxidation was a secondary pathway and was primarily catalyzed by CYP3A4/5 with a minor contribution from CYP2D6.

Excretion

Following oral administration of radiolabeled paltusotine, fecal excretion was the predominant route of elimination with observed mean recovery of total administered radioactivity being 90% in feces and 3.9% in urine. Unchanged paltusotine was a major component in excreta.

Specific Populations

Effects of Age, Body Weight, Sex, Race, Renal Function, and UGT1A1 Polymorphism

Based on population pharmacokinetics data, no clinically significant difference in the pharmacokinetics of paltusotine was observed based on age (18 to 84 years), body weight (45 to 138 kg), sex, race (White, Asian, Other), renal function (52 to 148 mL/min/1.73 m^2; eGFR), or UGT1A1 polymorphism.

Hepatic Impairment

Paltusotine AUC did not change in participants with mild hepatic impairment (Child-Pugh A) compared to participants with normal hepatic function. Paltusotine AUC decreased by 25% in moderate (Child-Pugh B) and 10% in severe (Child-Pugh C) hepatic impairment.

Drug Interaction Clinical Studies and Model-Informed Approaches

Effects of Other Drugs on PALSONIFY

Strong CYP3A4 Inducers:

Paltusotine Cmax and AUC decreased by approximately 44% and 70%, respectively, following concomitant administration of carbamazepine (a strong inducer of multiple enzymes and transporters [CYP3A4, UGT1A1, and P-gp]).

Moderate CYP3A4 Inducers:

Drugs such as efavirenz are predicted to decrease Cmax and AUC of paltusotine approximately 5% and 30%, respectively.

Proton Pump Inhibitors (PPIs):

Paltusotine exhibited pH-dependent aqueous solubility. Paltusotine AUC was decreased by 21% with 20 mg dose and 42% with 60 mg dose levels.

Other Drugs:

Weak CYP3A4 inducers or inhibitors of CYP3A4/5, P-gp, or UGT1A1 are predicted to not cause clinically significant changes in paltusotine pharmacokinetics.

Effects of PALSONIFY on Other Drugs

Cyclosporine:

Concomitant use of PALSONIFY decreased cyclosporine Cmax and AUC in whole blood by 53% and 35%, respectively.

Other Drugs:

Paltusotine did not show clinically significant changes in the pharmacokinetics of other drugs that were CYP3A4/5 or MATE substrates. Paltusotine is predicted to not cause clinically significant changes in the pharmacokinetics of other drugs that are CYP2D6 or P-gp substrates.

In Vitro Studies

In vitro studies suggest paltusotine is an inhibitor of CYP2D6, CYP3A4, and CYP2C19 and a weak inhibitor of UGT1A1, UGT1A3, and UGT1A9 but is unlikely to meaningfully inhibit these enzymes at clinically relevant concentrations. Paltusotine does not inhibit CYP1A2, CYP2B6, CYP2C8, CYP2C9, UGT1A6, or UGT2B15. Paltusotine is not an inducer of CYP1A2, CYP2B6, or CYP3A4.

Paltusotine is a substrate of P-gp and BCRP transporters. In vitro studies suggest paltusotine is an inhibitor of P-gp, MATE-1, MATE2-K, and BSEP transporters but is unlikely to meaningfully inhibit these transporters at clinically relevant concentrations. Paltusotine does not inhibit OAT1, OAT3, or OCT1.

13 NONCLINICAL TOXICOLOGY

13.1 Carcinogenesis, Mutagenesis, Impairment of Fertility

Carcinogenesis and Mutagenesis

No carcinogenic potential was demonstrated in transgenic (rasH2) mice when administering paltusotine by oral gavage for 26 weeks at doses up to 300 mg/kg/day (2.8-times the clinical dose of 60 mg based on AUC). Additionally, no carcinogenic effects were noted when administering paltusotine by oral gavage for 88 to 90 weeks at doses up to 500 mg/kg/day (34-times the clinical dose of 60 mg based on AUC) in rats. Paltusotine was not genotoxic in the in vitro bacterial reverse mutation test (Ames), in vitro micronucleus assay, or in the in vivo rat bone marrow micronucleus assay.

Impairment of Fertility

Animal studies have been conducted to evaluate the effect of paltusotine on fertility and early embryonic development of rats at doses of up to 500 mg/kg/day (18-times the clinical dose of 60 mg based on AUC). There were no paltusotine-related effects on any mating or fertility parameter in males or females at any dose. In addition, there were no paltusotine-related effects on reproductive organ weights or sperm parameters in males at any dose. Based on the finding of decreased corpora lutea in females at 500 mg/kg/day (which resulted in fewer implantation sites and live embryos/litter), the reproductive no-observed-adverse-effect-level (NOAEL) in females was considered to be 75 mg/kg/day (5-times the clinical dose of 60 mg based on AUC).

13.2 Phototoxicity

Paltusotine absorbs light at 203 to 350 nm wavelength and exhibited a positive phototoxicity signal in vitro as indicated by reduced viability of BALB/c 3T3 mouse fibroblasts. In a phototoxicity study in pigmented Long-Evans rats, oral administration of paltusotine for three consecutive days followed by ultraviolet radiation (UVR) exposure resulted in non-dose dependent ocular toxicities including corneal dystrophy, unilateral inferior focal retinopathy, and unilateral retinal degeneration/necrosis at systemic exposures approximately 2-times the exposure at the MRHD (based on body surface area). The clinical significance of these findings to humans is unknown.

14 CLINICAL STUDIES

The effectiveness of PALSONIFY for treatment of adults with acromegaly was evaluated in two randomized, double-blind, parallel group, placebo-controlled clinical studies.

14.1 Study 1: Adults with Acromegaly Naïve or Previously Treated on a Somatostatin Analog

Study 1 (NCT05192382) enrolled 111 adult participants with biochemically uncontrolled acromegaly. Participants were either treatment naïve (n=46/111) or had no treatment within the previous 4 months prior to screening (n=36/111) (‘Not Medically Treated’ group) or were previously treated on a somatostatin receptor analog and then washed out of treatment during screening (n=29/111) (‘Washout’ group). The mean age at enrollment was 47 years (range: 18 to 80 years); 53% were female; and 52% were White, 31% Asian, 3% Black or African American, 9% Other, and 5% Unknown race. The mean duration since diagnosis of acromegaly was 87 months. Prior to study participation, 95% of participants had received pituitary surgery (mean duration 78 months prior to study participation). Of the 111 participants, 86 (78%) had macroadenomas (>10 mm), 9 (8%) had microadenomas (≤10 mm), and tumor size was unknown in 16 (14%) participants. In the ‘Not Medically Treated’ group, IGF-1 levels were required to be ≥1.3×ULN at screening. In the ‘Washout’ group, IGF-1 levels were required to be ≤1.0×ULN at screening and ≥1.1×ULN with at least a 30% rise in IGF-1 after washout. Participants were randomized to receive either PALSONIFY (n=54) or placebo (n=57) for the 24-week treatment period.

Dose

The starting dose was 20 mg daily, followed by dose increase to 40 mg daily after 2 weeks. The dose could be titrated from 40 mg to a maximum dose of 60 mg based on IGF-1 value during the first 12 weeks of treatment. After Week 12, the PALSONIFY dose was maintained until the end of the randomized controlled period of the study (Week 24). The dose could be down titrated at any time during the study based on tolerability. Rescue therapy with standard of care treatment was initiated if a participant had evidence of uncontrolled acromegaly based on IGF-1 levels and symptoms. Fourteen (13%) participants received rescue therapy during the study: one (2%) participant in PALSONIFY arm and 13 (23%) participants in placebo arm.

Efficacy Assessment and Results

The primary endpoint was the proportion of PALSONIFY participants achieving biochemical control (defined as IGF-1 level ≤1.0×ULN) compared to placebo-treated participants. At Week 24, 56% of PALSONIFY participants achieved biochemical control compared to 5% of placebo-treated participants (p-value <0.0001) (Table 5).

Table 5. Proportion of Participants Achieving Biochemical Control (IGF-1 Levels ≤1.0×ULN) at Week 24 in Adults with Acromegaly (Study 1)
IGF-1 Normalization | PALSONIFY (N=54) | Placebo (N=57) | p-value
Proportion of participants who achieved response in IGF-1 at Week 24 (≤1.0×ULN)a | 56% | 5% | <0.0001
a The baseline mean IGF-1 was 2.3×ULN in the ‘Not Medically Treated’ group and 1.5×ULN in the ‘Washout’ group.
IGF-1=insulin-like growth factor-1; ULN=upper limit of normal
IGF-1 at Week 24 is based on the average of the last 2 measurements of IGF-1 collected at Weeks 22 and 24. When one of the two last IGF-1 measurements was missing a single value was used. Week 24 is the end of the randomized controlled portion of the study; if a participant received rescue therapy, the last assessment prior to rescue is used.

The majority of participants who achieved IGF-1 normalization during Study 1 did so within the first 2 to 4 weeks following initiation of treatment, with sustained response through the end of the treatment period.

A posthoc subgroup analysis for the primary efficacy endpoint evaluating the response rate in participants who were naïve to medical treatment, who had not achieved biochemical control on prior medical therapy, or for whom prior biochemical control status was unknown (Group A) and participants who demonstrated prior response to medical therapy who were either washed out from the previous therapy prior to baseline or had documented biochemical control on prior medical therapy (Group B) is provided below (Table 6).

Table 6. Proportion of Participants Achieving Biochemical Control (IGF-1 Levels ≤1.0×ULN) at Week 24 in Adults with Acromegaly Based on Prior Biochemical Control (Study 1)
IGF-1 Normalization | PALSONIFY (N=54) (n/Nx) | Placebo (N=57) (n/Nx) | Treatment Difference (95% CI) a
Group A: Treatment naïve, uncontrolled on prior therapy, or with unknown biochemical control on prior therapy(s) | 34% (11/32) | 3% (1/35) | 32% (11%, 51%)
Treatment naïve | 23% (5/22) | 4% (1/23) | 18% (-6%, 42%)
Absence of biochemical control on prior treatmentb | 57% (4/7) | 0% (0/6) | 57% (-4%, 88%)
Unknown biochemical control on prior treatmentc | 67% (2/3) | 0% (0/6) | 67% (-6%, 98%)
Group B: Responders to prior treatmentd | 86% (19/22) | 9% (2/22) | 77% (46%, 90%)
N=total number of participants per treatment arm; n=number of participants with event; Nx=total number of participants in the subgroup; CI=confidence interval
a Continuity-corrected Newcombe-Wilson confidence limits were used for the 95% confidence interval.
b Participants who were not medically treated recently and had not achieved biochemical control on previous medical therapy.
c Participants who were not medically treated recently and for whom biochemical control on previous medical therapy was unknown.
d Participants who were either washed out or not medically treated recently but had achieved biochemical control on previous medical therapy.

In Study 1, PALSONIFY-treated participants had numerically lower (versus placebo) severity of symptom scores associated with acromegaly as measured by the patient-reported symptom severity instrument, which assessed headaches, joint pain, sweating, fatigue, weakness, swelling, and/or numbness/tingling.

14.2 Study 2: Adults with Acromegaly Previously Controlled on a Somatostatin Analog

Study 2 (NCT04837040) enrolled 58 participants who were previously biochemically controlled (defined as IGF-1 levels ≤1.0×ULN during screening and at randomization) on injectable depot octreotide or lanreotide somatostatin analog formulations. The mean age at enrollment was 55 years (range: 29 to 84 years); 55% were female; and 72% were White, 3% Asian, 5% Black or African American, 12% Other, and 7% Unknown race. The mean duration since diagnosis of acromegaly was 155 months. Prior to study participation, 86% of participants had received pituitary surgery (mean duration 138 months prior to study participation). Of the 58 participants, 33 (57%) had macroadenomas (>10 mm), 11 (19%) had microadenomas (≤10 mm), and tumor size was unknown in 14 (24%) participants. Participants were randomized to receive either PALSONIFY (n=30) or placebo (n=28) for the 36-week treatment period.

Dose

The starting dose was 40 mg, and the dose could be titrated from 40 mg to a maximum of 60 mg based on IGF-1 value during the first 24 weeks of treatment. After Week 24, the PALSONIFY dose was maintained until the end of the randomized controlled period of the study (Week 36). The dose could be down titrated at any time during the study based on tolerability. Rescue therapy with standard of care treatment was initiated if a participant had evidence of uncontrolled acromegaly based on IGF-1 levels and symptoms. Eighteen (31%) participants received rescue therapy during the study: one (3%) participant in PALSONIFY arm and 17 (61%) participants in placebo arm.

Efficacy Assessment and Results

The primary endpoint was the proportion of PALSONIFY participants with biochemical response maintenance (i.e., IGF-1 ≤1.0×ULN) compared to placebo-treated participants. At Week 36, 83% of PALSONIFY participants maintained biochemical control compared to 4% of placebo-treated participants (p-value <0.0001) (Table 7).

Table 7. Proportion of Participants Maintaining Biochemical Control (IGF-1 Levels ≤1.0×ULN) in Adults with Acromegaly and Previously Maintained on a Somatostatin Analog Injection (Study 2)
IGF-1 Normalization | PALSONIFY (N=30) | Placebo (N=28) | p-value
Proportion of participants who maintained response in IGF-1 at Week 36 (≤1.0×ULN)a | 83% | 4% | <0.0001
a The baseline mean IGF-1 was 0.83×ULN. Of enrolled participants, 59% were previously treated with octreotide and 41% previously treated with lanreotide.
IGF-1=insulin-like growth factor-1; ULN=upper limit of normal
Week 36 is the end of the randomized controlled portion of the study; if a participant received rescue therapy, the last assessment prior to rescue is used.

In Study 2, PALSONIFY-treated participants had numerically lower (versus placebo) severity of symptom scores associated with acromegaly as measured by the patient-reported symptom severity instrument, which assessed headaches, joint pain, sweating, fatigue, weakness, swelling, and/or numbness/tingling.

16 HOW SUPPLIED/STORAGE AND HANDLING

How Supplied

PALSONIFY is provided in two strengths: 20 mg and 30 mg.

Table 8. PALSONIFY Configurations and NDC Numbers
Strength | Tablet Color/Shape | Imprint | NDC | Package Size
20 mg | Pink; biconvex oval shape | “PAL” on one side; “20” on other side | 84015-920-60 | Bottle of 60 tablets
30 mg | Yellow; biconvex oval shape | “PAL” on one side; “30” on other side | 84015-930-60 | Bottle of 60 tablets

Storage and Handling

- PALSONIFY tablets are packaged in a child-resistant container; keep out of reach of children.
- Store tablets at 20°C to 25°C (68°F to 77°F) [see USP Controlled Room Temperature]. Excursions permitted 15°C to 30°C (59°F to 86°F).
- Store and dispense in original container or USP equivalent tight container.

17 PATIENT COUNSELING INFORMATION

Advise the patient to read the FDA-approved patient labeling (Patient Information).

Cholelithiasis and its Complications

Advise patients to contact their healthcare provider if they experience signs or symptoms of gallstones (cholelithiasis) or complications of cholelithiasis (e.g., cholecystitis, cholangitis, and pancreatitis) [see Warnings and Precautions (5.1)].

Hyperglycemia and Hypoglycemia

Advise patients to contact their healthcare provider if they have problems with blood sugar levels, either hyperglycemia or hypoglycemia [see Warnings and Precautions (5.2)].

Cardiovascular Abnormalities

Advise patients to contact their healthcare provider if they notice irregular heartbeat [see Warnings and Precautions (5.3)].

Thyroid Function Abnormalities

Advise patients that their thyroid function may be assessed periodically [see Warnings and Precautions (5.4)].

Steatorrhea and Malabsorption of Dietary Fats

Advise patients to contact their healthcare provider if they experience new or worsening symptoms of steatorrhea, loose stools, abdominal bloating, weight loss [see Warnings and Precautions (5.5)].

Vitamin B 12 Deficiency

Advise patients that Vitamin B12 levels may be monitored during treatment [see Warnings and Precautions (5.6)].

PALSONIFY is a trademark of Crinetics Pharmaceuticals, Inc.
©2025 Crinetics Pharmaceuticals, Inc. All rights reserved.
Manufactured for:
Crinetics Pharmaceuticals, Inc.
San Diego, CA 92121 USA

Patient Information
PALSONIFY™ [pal-SAHN-ih-fy]
(paltusotine)
tablets, for oral use

What is PALSONIFY?

- PALSONIFY is a prescription medicine used to treat adults with acromegaly for whom surgery was not effective or surgery is not an option.
- It is not known if PALSONIFY is safe and effective in children.

Before you take PALSONIFY, tell your healthcare provider about all of your medical conditions, including if you:

- have gallbladder problems.
- have blood sugar control problems (low blood sugar or high blood sugar).
- have problems with low heart rate.
- are pregnant or plan to become pregnant. It is not known if PALSONIFY will harm your unborn baby.
- are breastfeeding or plan to breastfeed. It is not known if PALSONIFY passes into your breast milk. Talk to your healthcare provider about the best way to feed your baby if you take PALSONIFY.

Tell your healthcare provider about all the medicines you take, including prescription and over-the-counter medicines, vitamins, and herbal supplements. PALSONIFY may affect the way other medicines work, and other medicines may affect how PALSONIFY works.
Especially tell your healthcare provider if you take medicine that can slow the heart rate.
Know the medicines you take. Keep a list of them to show your healthcare provider and pharmacist when you get a new medicine.

How should I take PALSONIFY?

- Take PALSONIFY exactly as your healthcare provider tells you to take it.
- Take PALSONIFY by mouth 1 time a day with a glass of water on an empty stomach.
- Take PALSONIFY at least 6 hours after a meal (for example, after an overnight fast) and at least 1 hour before the next meal.

What are the possible side effects of PALSONIFY?
PALSONIFY may cause serious side effects including:

- gallbladder problems. PALSONIFY may cause problems with the gallbladder. Tell your healthcare provider if you have sudden pain in the upper right area of your stomach (abdomen), sudden pain in your right shoulder or between your shoulder blades, yellowing of your skin or the whites of your eyes, or pale stools.
- blood sugar problems. PALSONIFY may change hormone levels that can lead to high blood sugar (hyperglycemia), low blood sugar (hypoglycemia), or diabetes. Tell your healthcare provider if you have problems with high or low blood sugar. Your healthcare provider will check your blood sugar when you start taking PALSONIFY or when your dose is changed.
- heart rate problems. Tell your healthcare provider if your heart is not beating normally.
- thyroid problems. PALSONIFY may keep your thyroid from releasing thyroid hormones, leading to hypothyroidism. Your thyroid function may be checked from time to time during your treatment with PALSONIFY.
- fatty stools. PALSONIFY may cause your body to have problems with absorbing dietary fats. Tell your healthcare provider if you have any new or worsening symptoms including fatty stools, changes in the color of your stools, loose stools, stomach (abdominal) bloating, or weight loss.
- low vitamin B 12 levels in your blood. Your healthcare provider may check your vitamin B12 levels during treatment with PALSONIFY.

The most common side effects of PALSONIFY include:

- diarrhea
- stomach area (abdominal) pain
- nausea and vomiting
- decreased appetite

- slow heart rate (bradycardia)
- high blood sugar levels (hyperglycemia)
- irregular heartbeat (palpitations)

These are not all the possible side effects of PALSONIFY. For more information, ask your healthcare provider or pharmacist.
Call your doctor for medical advice about side effects of PALSONIFY. You may report side effects to FDA at 1-800-FDA-1088.

How should I store PALSONIFY?

- Store PALSONIFY at room temperature between 68°F to 77°F (20°C to 25°C).
- Store PALSONIFY in the original container.

Keep PALSONIFY and all medicines out of the reach of children.

General information about the safe and effective use of PALSONIFY.
Medicines are sometimes prescribed for purposes other than those listed in the Patient Information leaflet. Do not use PALSONIFY for a condition for which it was not prescribed. Do not give PALSONIFY to other people, even if they have the same symptoms you have. It may harm them. You can ask your pharmacist or healthcare provider for information about PALSONIFY that is written for health professionals.

What are the ingredients in PALSONIFY?
Active ingredient: paltusotine
Inactive ingredients: colloidal silicon dioxide, copovidone, crospovidone, magnesium stearate, mannitol, and microcrystalline cellulose. Additionally, the 20 mg tablets contain Opadry pink coating (hypromellose, iron oxide red, iron oxide yellow, titanium dioxide, and triacetin) and the 30 mg tablets contain Opadry yellow coating (hypromellose, iron oxide yellow, titanium dioxide, and triacetin).
Manufactured for:
Crinetics Pharmaceuticals, Inc.
San Diego, California 92121
For more information about PALSONIFY call 1-833-CRN-INFO (1-833-276-4636) or go to www.PALSONIFY.com.

This Patient Information has been approved by the U.S. Food and Drug Administration

Issued: 09/2025

PACKAGE LABEL

Principal Display Panel

NDC 84015-920-60

Rx Only

Once-Daily Oral

Palsonify™

(paltusotine) tablets

20 mg

60 Tablets

PACKAGE LABEL

Principal Display Panel

NDC 84015-930-60

Rx Only

Once-Daily Oral

Palsonify™

(paltusotine) tablets

30 mg

60 Tablets